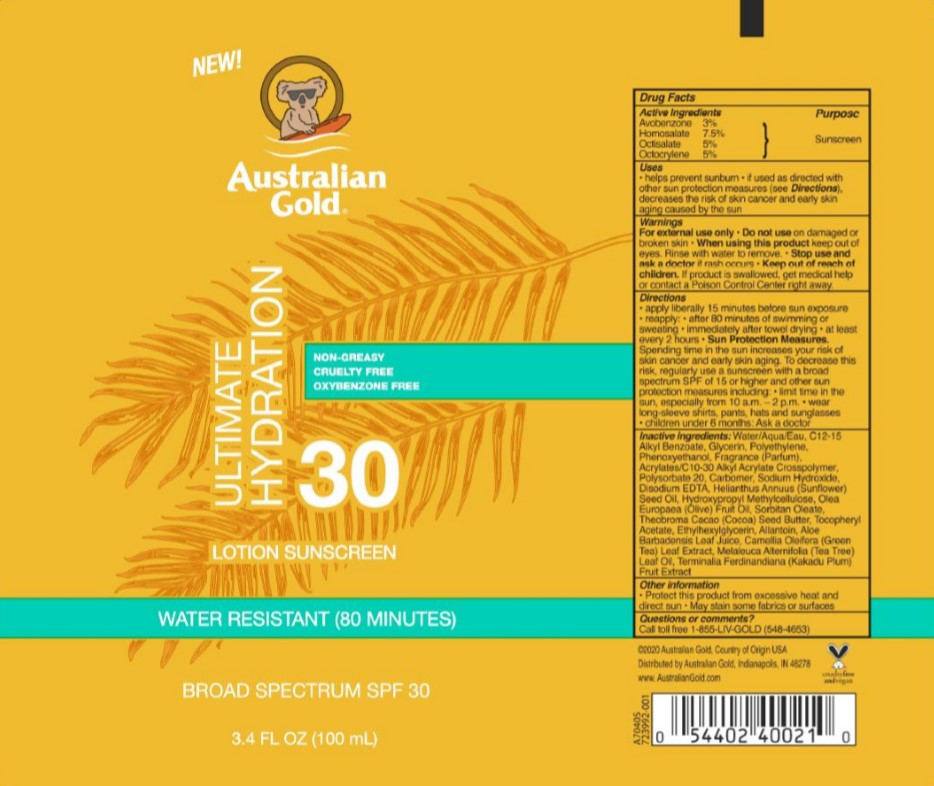 DRUG LABEL: Australian Gold
NDC: 58443-0382 | Form: LOTION
Manufacturer: Prime Enterprises, Inc.
Category: otc | Type: HUMAN OTC DRUG LABEL
Date: 20210106

ACTIVE INGREDIENTS: OCTOCRYLENE 51.45 mg/1 mL; AVOBENZONE 30.87 mg/1 mL; HOMOSALATE 77.175 mg/1 mL; OCTISALATE 51.45 mg/1 mL
INACTIVE INGREDIENTS: CARBOMER INTERPOLYMER TYPE A (ALLYL SUCROSE CROSSLINKED); POLYSORBATE 20; OLIVE OIL; SORBITAN MONOOLEATE; COCOA BUTTER; TEA TREE OIL; KAKADU PLUM; WATER; ALKYL (C12-15) BENZOATE; GLYCERIN; PHENOXYETHANOL; CARBOMER HOMOPOLYMER, UNSPECIFIED TYPE; SODIUM HYDROXIDE; EDETATE DISODIUM ANHYDROUS; SUNFLOWER OIL; HYPROMELLOSE, UNSPECIFIED; ALPHA-TOCOPHEROL ACETATE; ETHYLHEXYLGLYCERIN; ALOE VERA LEAF; HIGH DENSITY POLYETHYLENE; ALLANTOIN; CAMELLIA OLEIFERA LEAF

Australian Gold Ultimate Hydration Lotion Sunscreen SPF 30

Active Ingredients

Avobenzone 3%

Homosalate 7.5%

Octisalate 5%

Octocrylene 5%

Purpose

Sunscreen

Uses

helps prevent sunburn

if used as directed with other sun protection measures (see Directions), decreases the risk of skin cancer and early skin aging caused by the sun

Warnings

For external use only

Do not use

on damaged or broken skin

When using this product

keep out eyes. Rinse with water to remove.

Stop use and ask a doctor

if rash occurs

Keep out of reach of children

If product is swallowed, get medial help or contact a Poison Control Center right away.

Directions

apply liberally 15 minutes before sun exposure

reapply

after 80 minutes of swimming or sweating

immediately after towel drying

at least every 2 hours

Sun Protection Measures. Spending time in the sun increases your risk of skin cancer and early skin aging. To decrease this risk, regularly use a sunscreen with a broad spectrum SPF of 15 or higher and other sun protection measures including: limit time in the sun, especially from 10 a.m. - 2 p.m.

wear long-sleeve shirts, pants, hats and sunglasses

children under 6 months: Ask a doctor

Inactive ingredients

Water, C12-15 Alkyl Benzoate, Glycerin, Polyethylene, Phenoxyethanol, Fragrance, Acrylates/C10-30 Alkyl Acrylate Crosspolymer, Polysorbate 20, Carbomer, Sodium Hydroxide, Disodium EDTA, Helianthus Annuus (Sunflower) Seed Oil, Hydroxypropyl Methylcellulose, Olea Europaea (Olive) Fruit Oil, Sorbitan Oleate, Theobroma Cacao (Cocoa) Seed Butter, Tocopheryl Acetate, Ethylhexylglycerin, Allantoin, Aloe Barbadensis Leaf Juice, Camellia Oleifera (Green Tea) Leaf Extract, Melaleuca Alternifolia (Tea Tree) Leaf Oil, Terminalia Ferdinandiana (Kakadu Plum) Fruit Extract

Other information

Protect this product form excessive heat and direct sun

May stain some fabrics or surfaces

Questions or comments?

Call toll free 1-855-LIV-GOLD (548-4653)